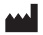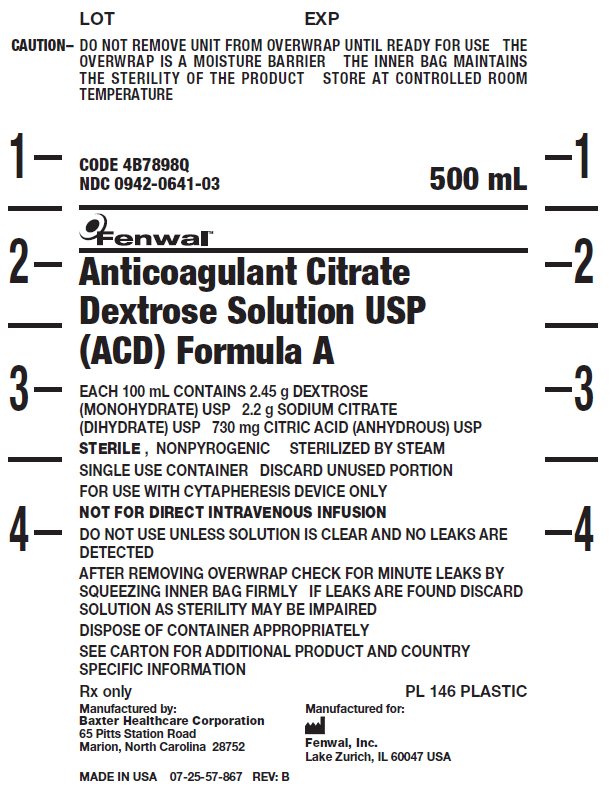 DRUG LABEL: ACD-A
NDC: 0942-0641 | Form: SOLUTION
Manufacturer: Fenwal, Inc.
Category: prescription | Type: HUMAN PRESCRIPTION DRUG LABEL
Date: 20220211

ACTIVE INGREDIENTS: Dextrose Monohydrate 12.25 g/500 mL; SODIUM CITRATE, UNSPECIFIED FORM 11 g/500 mL; Anhydrous Citric Acid 3.65 g/500 mL
INACTIVE INGREDIENTS: Water

Anticoagulant Citrate Dextrose Solution USP (ACD) Formula A

CAUTION–

DO NOT REMOVE UNIT FROM OVERWRAP UNTIL READY FOR USE
THE OVERWRAP IS A MOISTURE BARRIER
THE INNER BAG MAINTAINS THE STERILITY OF THE PRODUCT
STORE AT CONTROLLED ROOM TEMPERATURE

CODE 4B7898Q
NDC 0942-0641-03

500 mL

Fenwal™

Anticoagulant Citrate Dextrose Solution USP (ACD) Formula A

EACH 100 mL CONTAINS 2.45 g DEXTROSE (MONOHYDRATE) USP 2.2 g SODIUM CITRATE (DIHYDRATE) USP 730 mg CITRIC ACID (ANHYDROUS) USP

STERILE , NONPYROGENIC

STERILIZED BY STEAM

SINGLE USE CONTAINER

DISCARD UNUSED PORTION

FOR USE WITH CYTAPHERESIS DEVICE ONLY

NOT FOR DIRECT INTRAVENOUS INFUSION

DO NOT USE UNLESS SOLUTION IS CLEAR AND NO LEAKS ARE DETECTED

AFTER REMOVING OVERWRAP CHECK FOR MINUTE LEAKS BY SQUEEZING INNER BAG FIRMLY

IF LEAKS ARE FOUND DISCARD SOLUTION AS STERILITY MAY BE IMPAIRED

DISPOSE OF CONTAINER APPROPRIATELY

SEE CARTON FOR ADDITIONAL PRODUCT AND COUNTRY SPECIFIC INFORMATION

Rx only

PL 146 PLASTIC

Manufactured by:
Baxter Healthcare Corporation
65 Pitts Station Road
Marion, North Carolina 28752

MADE IN USA 07-25-57-867 REV: B

Manufactured for:

Fenwal, Inc.
Lake Zurich, IL 60047 USA

PACKAGE/LABEL DISPLAY PANEL

[Enter Package/Label Display Panel here]